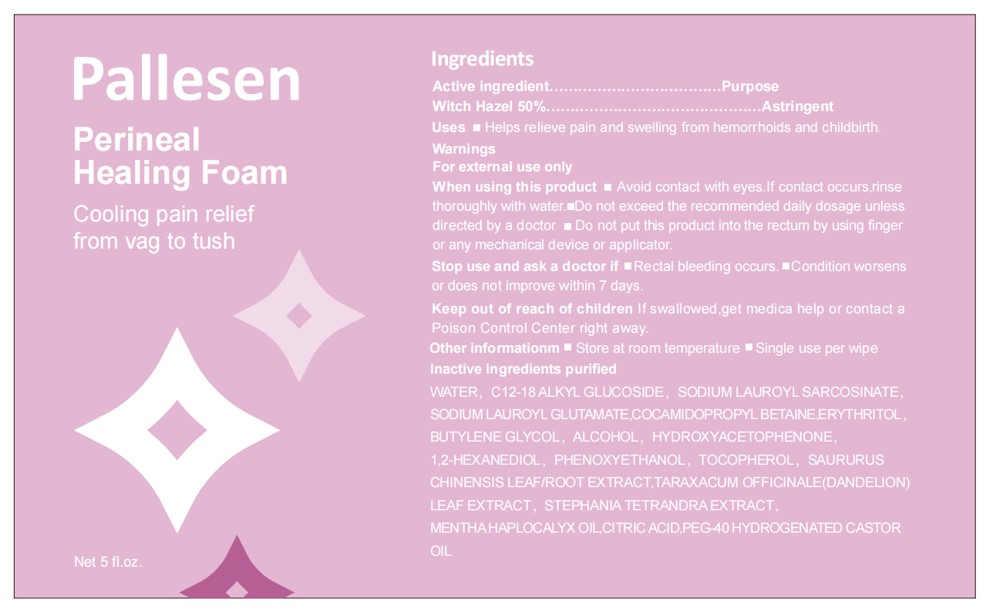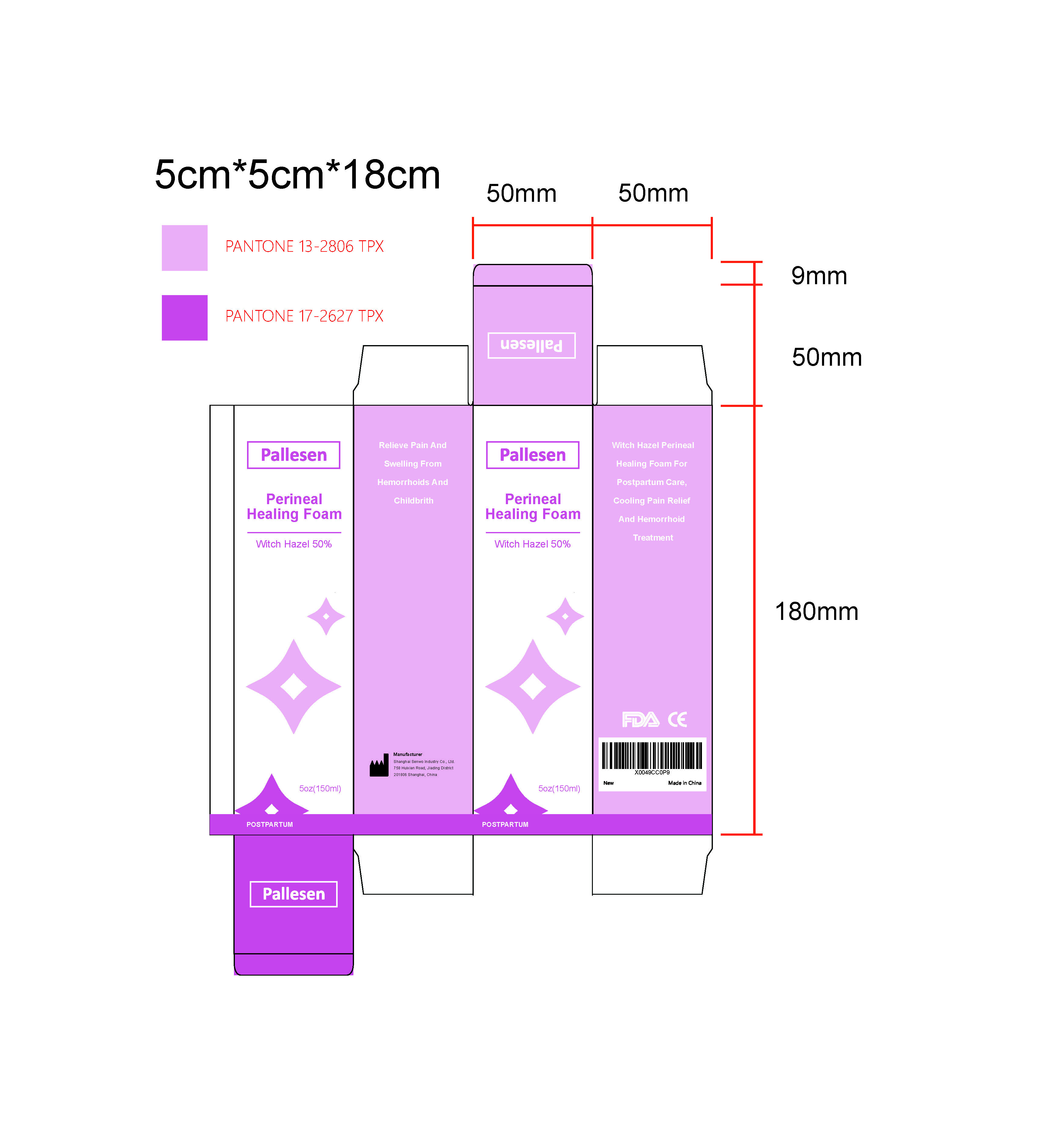 DRUG LABEL: Hazel Perineal Healing Foam
NDC: 85448-001 | Form: LIQUID
Manufacturer: Jiangsu Senwo Medical Technology Co., Ltd.
Category: otc | Type: HUMAN OTC DRUG LABEL
Date: 20251107

ACTIVE INGREDIENTS: WITCH HAZEL 50 g/100 mL
INACTIVE INGREDIENTS: COCAMIDOPROPYL BETAINE; 1,2-HEXANEDIOL; HYDROXYACETOPHENONE; TARAXACUM OFFICINALE; ANHYDROUS CITRIC ACID; POLYOXYL 40 HYDROGENATED CASTOR OIL; WATER; SODIUM LAUROYL GLUTAMATE; ERYTHRITOL; ALCOHOL; STEPHANIA TETRANDRA WHOLE; SODIUM LAUROYL SARCOSINATE; BUTYLENE GLYCOL; PEPPERMINT OIL; PHENOXYETHANOL; TOCOPHEROL; SAURURUS CHINENSIS WHOLE

85448-001 Hazel Perineal Healing Foam

ACTIVE INGREDIENT

Witch Hazel 50%

PURPOSE

Astringent

Keep out of reach of children lfswallowed,get medica help or contact aPoison Control Center right away.

INDICATIONS AND USAGE

Helps relieve pain and swelling from hemorrhoids and childbirth.

WARNINGS

For external use only

When using this product m Avoid contact with eyes.lf contact occurs.rinsethoroughly with water..Do not exceed the recommended daily dosage unlessdirected by a doctor m Do not put this product into the rectum by using fingeror any mechanical device or applicator.

STORAGE AND HANDLING

Other informationm Store at room temperature Single use per wipe

INACTIVE INGREDIENT

Water
C12-18 ALKYL GLUCOSIDE
SODIUM LAUROYL SARCOSINATE
SODIUM LAUROYL GLUTAMATE
COCAMIDOPROPYL BETAINE
ERYTHRITOL
BUTYLENE GLYCOL
ALCOHOL
HYDROXYACETOPHENONE
1,2-HEXANEDIOL
PHENOXYETHANOL
TOCOPHEROL
SAURURUS CHINENSIS LEAF/ROOT
EXTRACT
TARAXACUM OFFICINALE
(DANDELION) LEAF EXTRACT
STEPHANIA TETRANDRA EXTRACT
MENTHA HAPLOCALYX OIL
CITRIC ACID
PEG-40 HYDROGENATED CASTOR OIL